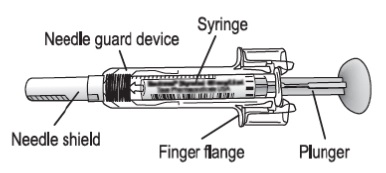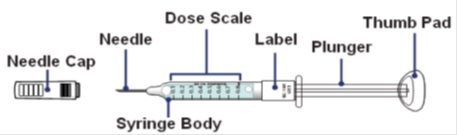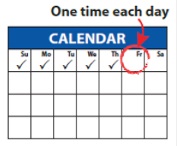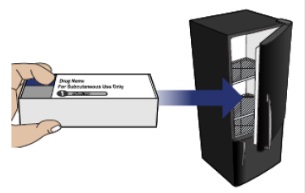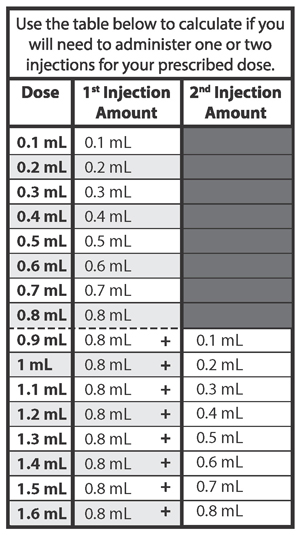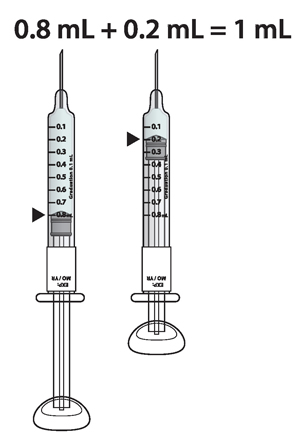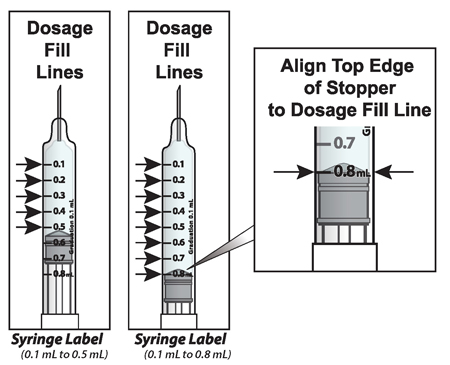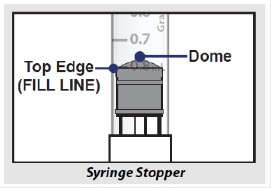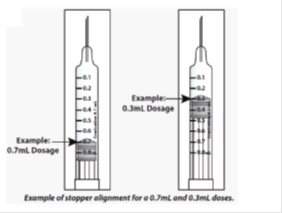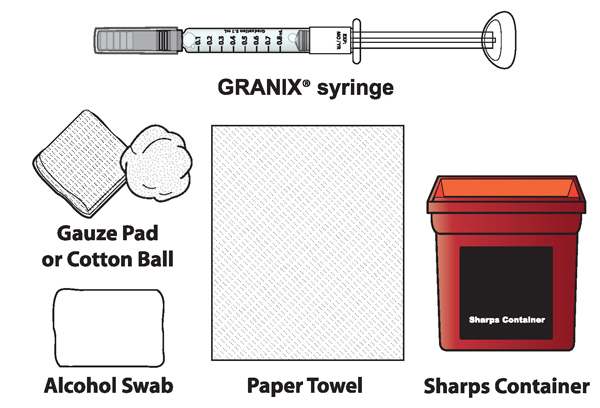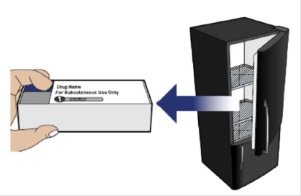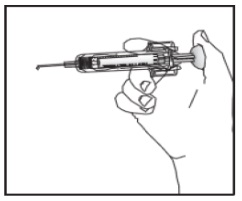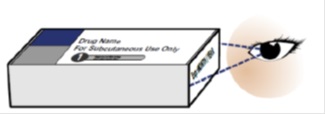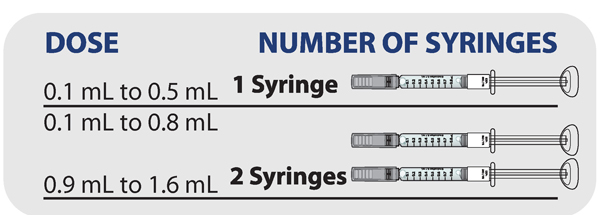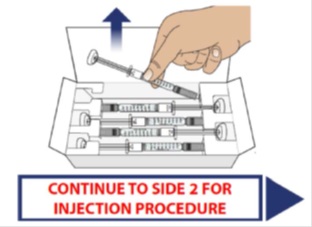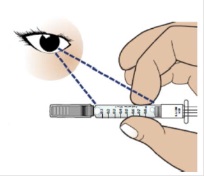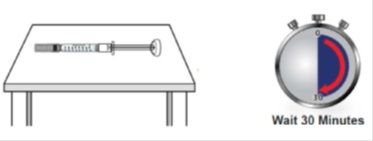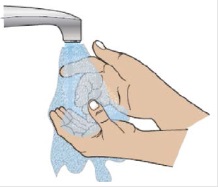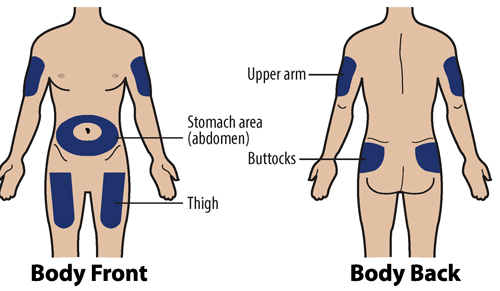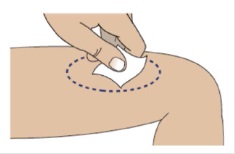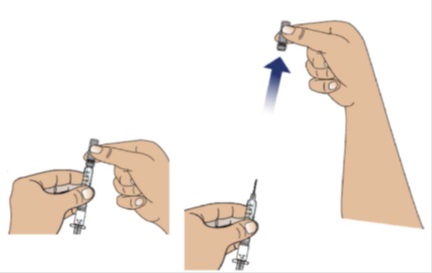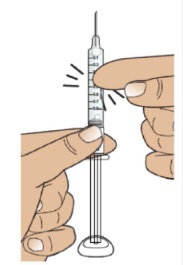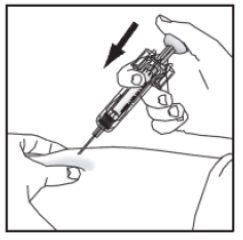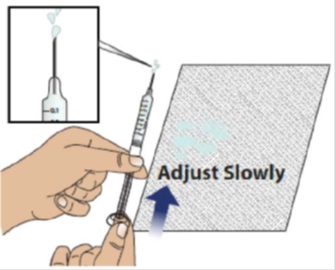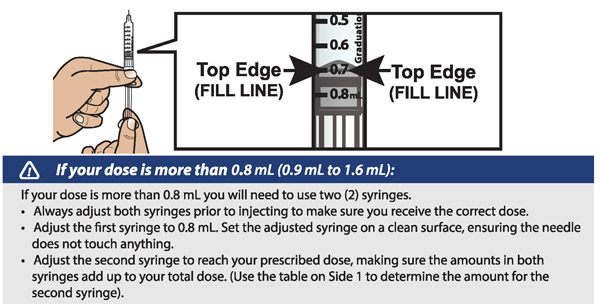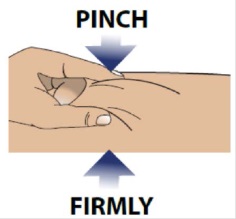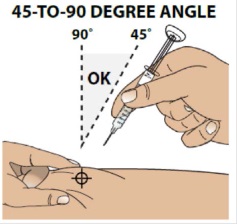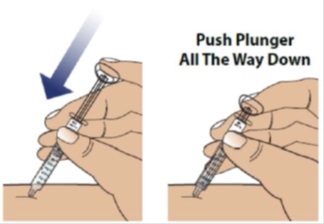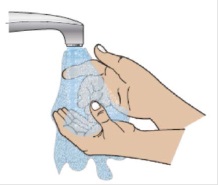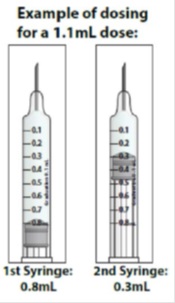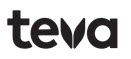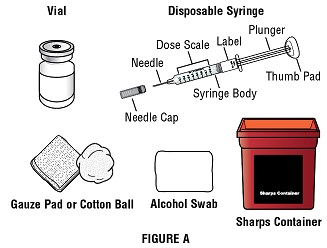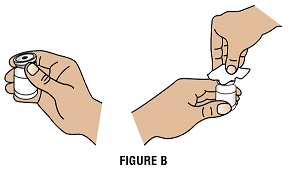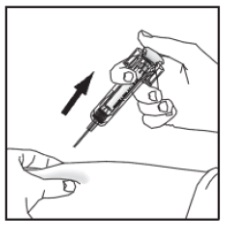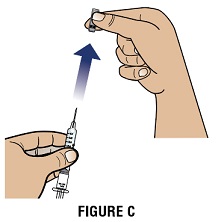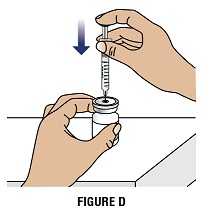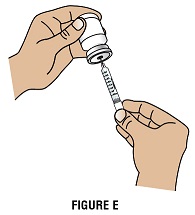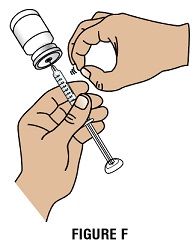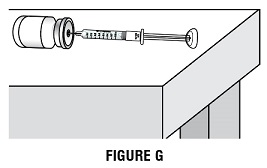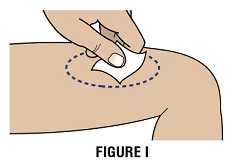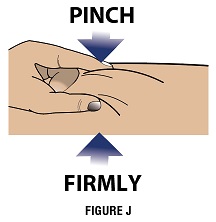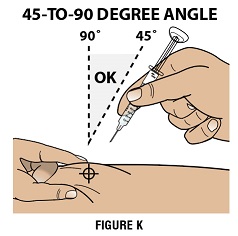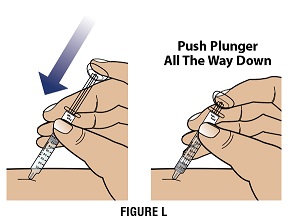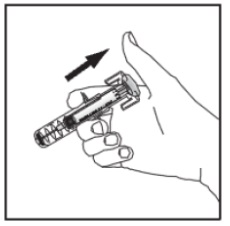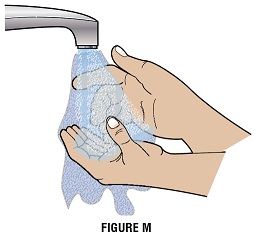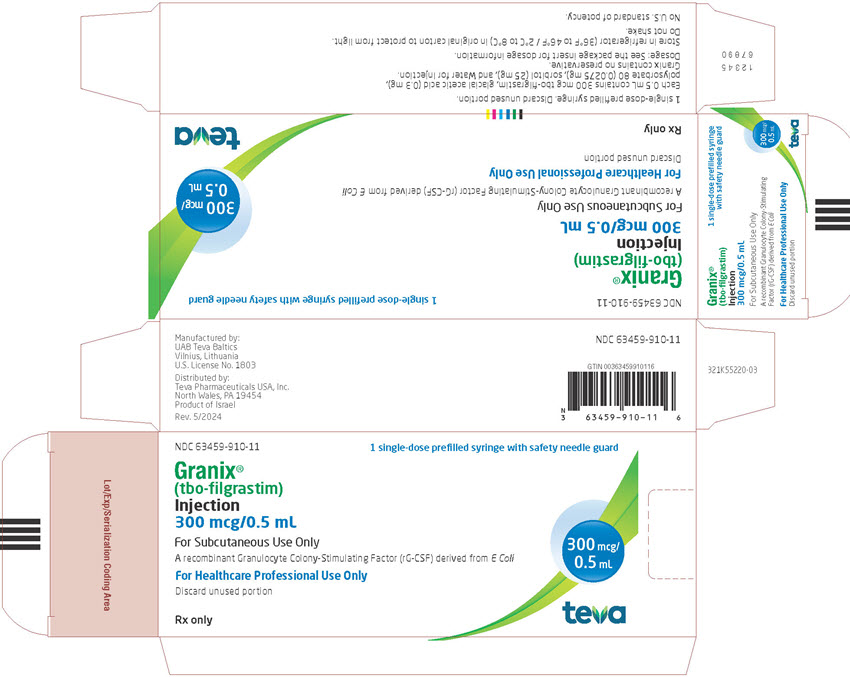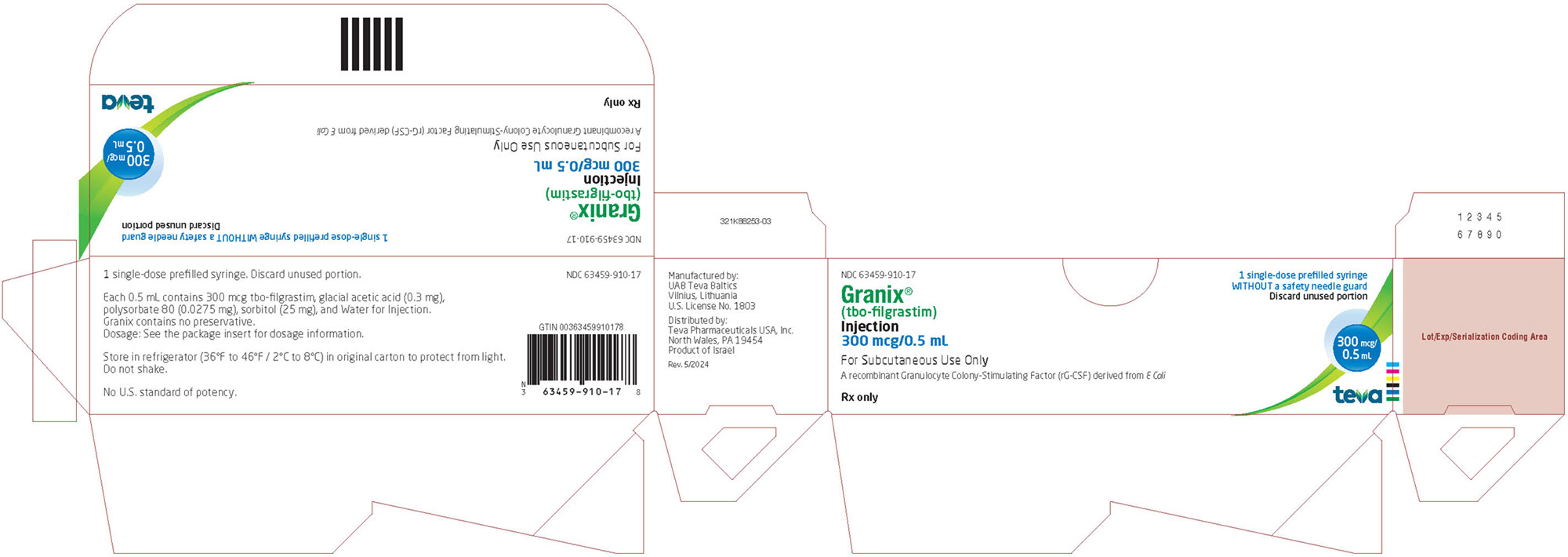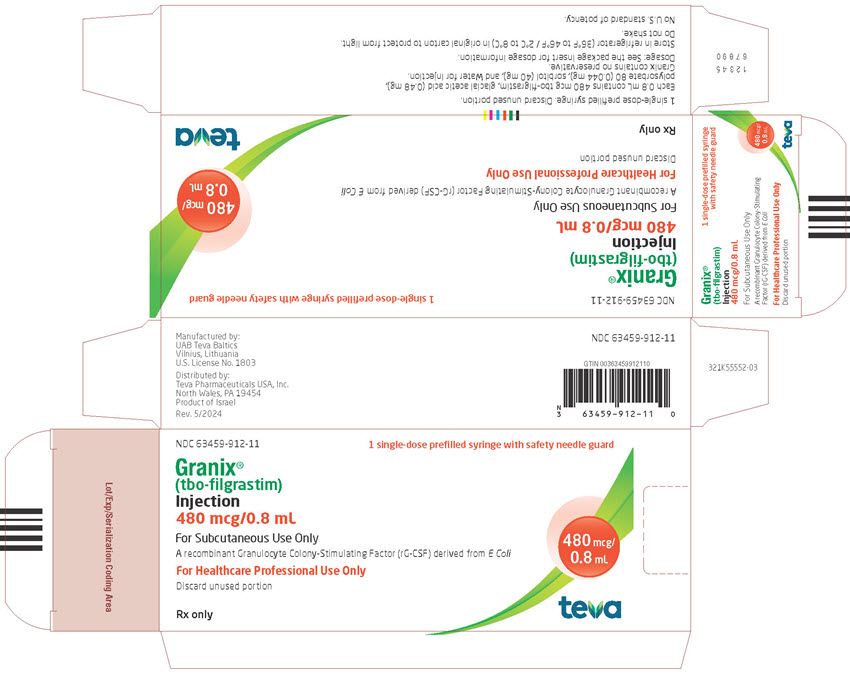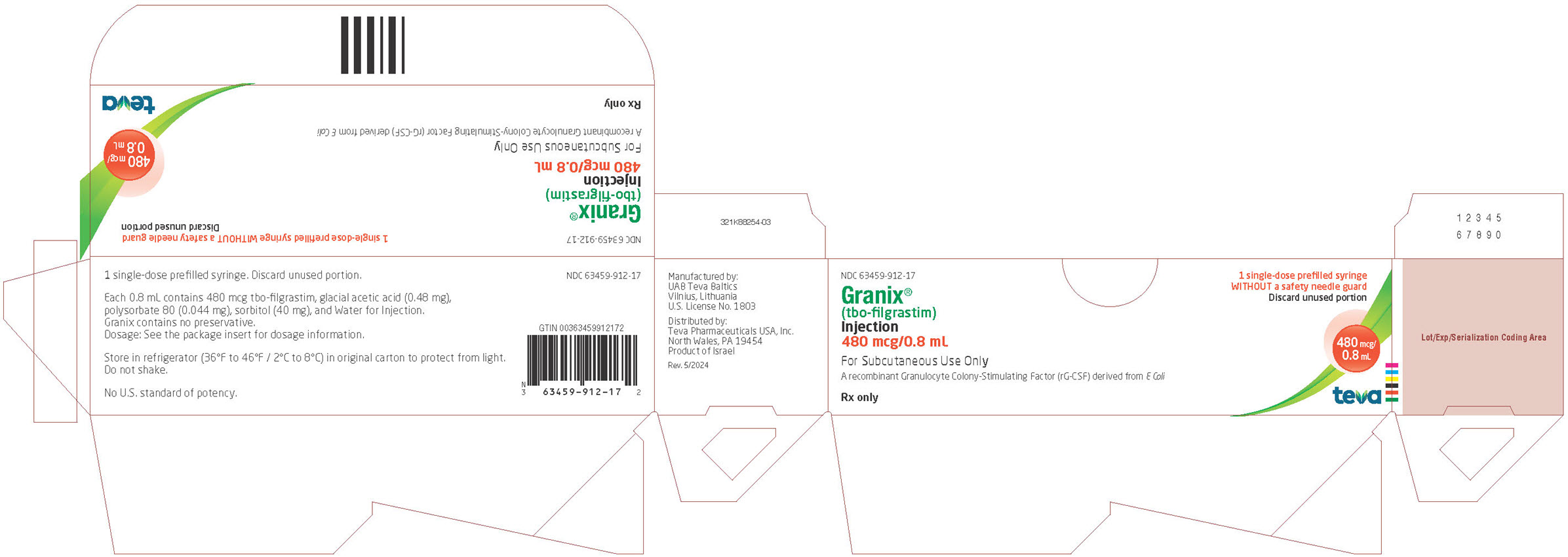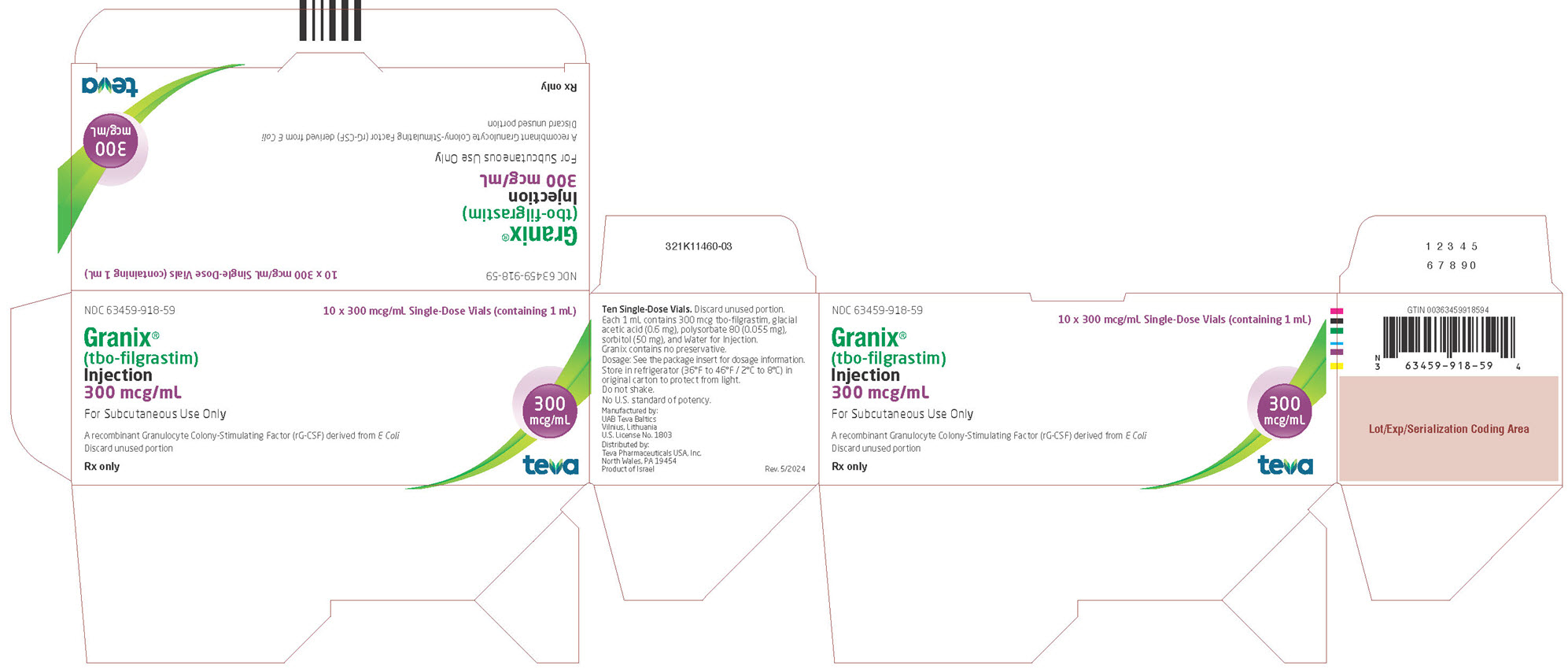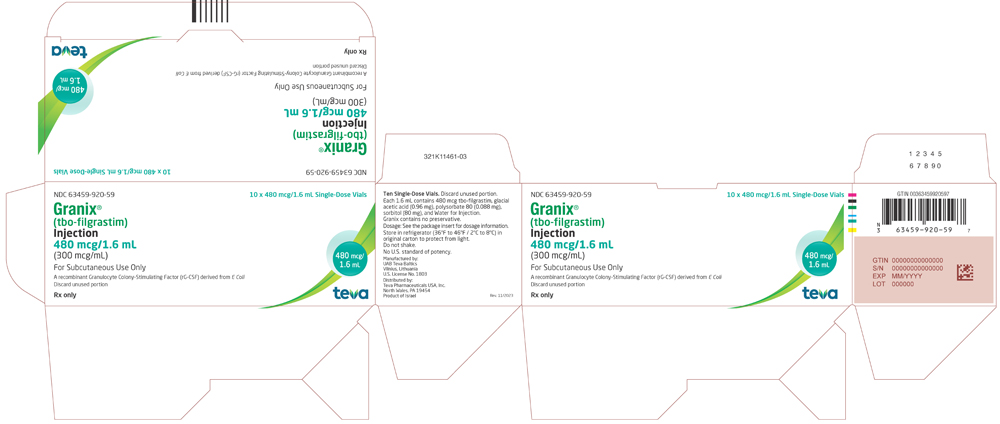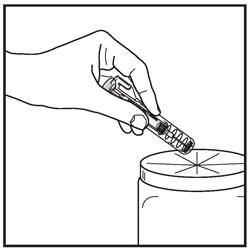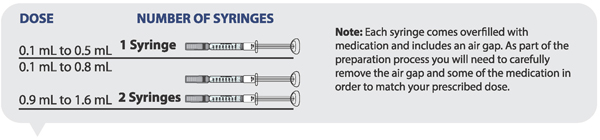 DRUG LABEL: GRANIX
NDC: 63459-910 | Form: INJECTION, SOLUTION
Manufacturer: Cephalon, LLC
Category: prescription | Type: HUMAN PRESCRIPTION DRUG LABEL
Date: 20231130

ACTIVE INGREDIENTS: FILGRASTIM 300 ug/0.5 mL
INACTIVE INGREDIENTS: ACETIC ACID; SORBITOL; POLYSORBATE 80; SODIUM HYDROXIDE; WATER

HIGHLIGHTS OF PRESCRIBING INFORMATION

These highlights do not include all the information needed to use GRANIX safely and effectively. See full prescribing information for GRANIX.
GRANIX® (tbo-filgrastim) injection, for subcutaneous use
Initial U.S. Approval: 2012

RECENT MAJOR CHANGES

Warnings and Precautions,
Myelodysplastic Syndrome and Acute Myeloid Leukemia
in Patients with Breast and Lung Cancer (5.8) 11/2023

1 INDICATIONS AND USAGE

GRANIX (tbo-filgrastim) is a leukocyte growth factor indicated in adult and pediatric patients 1 month and older for reduction in the duration of severe neutropenia in patients with non-myeloid malignancies receiving myelosuppressive anticancer drugs associated with a clinically significant incidence of febrile neutropenia. (1)

2 DOSAGE AND ADMINISTRATION

- Recommended dose: 5 mcg/kg per day administered as a subcutaneous injection
- Administer the first dose no earlier than 24 hours following myelosuppressive chemotherapy. Do not administer within 24 hours prior to chemotherapy (2.1)

3 DOSAGE FORMS AND STRENGTHS

Prefilled Syringe

- Injection: 300 mcg/0.5 mL solution in single-dose prefilled syringe (3)
- Injection: 480 mcg/0.8 mL solution in single-dose prefilled syringe (3)

Vial

- Injection: 300 mcg/mL solution in single-dose vials (3)
- Injection: 480 mcg/1.6 mL (300 mcg/mL) solution in single-dose vials (3)

4 CONTRAINDICATIONS

Patients with a history of serious allergic reactions to filgrastim products or pegfilgrastim products. (4)

5 WARNINGS AND PRECAUTIONS

- Splenic Rupture: Evaluate patients who report left upper abdominal or shoulder pain for an enlarged spleen or splenic rupture (5.1)
- Acute Respiratory Distress Syndrome (ARDS): Monitor for and manage immediately. Discontinue GRANIX if suspected (5.2)
- Serious Allergic Reactions Including Anaphylaxis: Permanently discontinue GRANIX in patients with serious allergic reactions (5.3)
- Sickle Cell Disorders: Severe and sometimes fatal crisis can occur. Discontinue GRANIX if suspected (5.4)
- Glomerulonephritis: Evaluate and consider dose reduction or interruption of GRANIX if causality is likely (5.5)
- Capillary Leak Syndrome: Monitor if symptoms develop and administer standard symptomatic treatment (5.6)
- Myelodysplastic Syndrome (MDS) and Acute Myeloid Leukemia (AML): Monitor patients with breast and lung cancer using GRANIX in conjunction with chemotherapy and/or radiotherapy for signs and symptoms of MDS/AML. (5.8)

6 ADVERSE REACTIONS

- Most common adverse reaction (≥1%) to GRANIX is bone pain (6.1)

To report SUSPECTED ADVERSE REACTIONS, contact Teva Pharmaceuticals at 1‑866-832-8537 or FDA at 1-800-FDA-1088 or www.fda.gov/medwatch.

8 USE IN SPECIFIC POPULATIONS

GRANIX should be used during pregnancy only if the potential benefit justifies the potential risk to the fetus. (8.1)

FULL PRESCRIBING INFORMATION

1 INDICATIONS AND USAGE

GRANIX is indicated to reduce the duration of severe neutropenia in adult and pediatric patients 1 month and older with non-myeloid malignancies receiving myelosuppressive anticancer drugs associated with a clinically significant incidence of febrile neutropenia.

2 DOSAGE AND ADMINISTRATION

2.1 Recommended Dosage

The recommended dose of GRANIX is 5 mcg/kg per day administered as a subcutaneous injection. Administer the first dose of GRANIX no earlier than 24 hours following myelosuppressive chemotherapy. Do not administer GRANIX within 24 hours prior to chemotherapy.

Daily dosing with GRANIX should continue until the expected neutrophil nadir is passed and the neutrophil count has recovered to the normal range. Monitor complete blood count (CBC) prior to chemotherapy and twice per week until recovery.

2.2 General Considerations for Administration

GRANIX may be administered by either a healthcare professional, a patient or caregiver. Before a decision is made to allow GRANIX to be administered by a patient or caregiver, ensure that the patient is an appropriate candidate for self-administration or administration by a caregiver. Proper training on storage, preparation, and administration technique should be provided. If a patient or caregiver is not an appropriate candidate for any reason, then in such patients, GRANIX should be administered by a healthcare professional.

Dispense only the prefilled syringe without a safety needle guard device to patient or caregiver. Instruct patients and caregivers to follow the Instructions for Use provided with the GRANIX prefilled syringe to properly administer an injection after training by a healthcare professional.

Visually inspect parenteral drug products for particulate matter and discoloration prior to administration. Do not administer GRANIX if discoloration or particulates are observed.

The prefilled syringe and vial are for single-dose only. Discard unused portions. GRANIX and all its components are not made with natural rubber latex.

Recommended sites for subcutaneous GRANIX injections include the abdomen (except for the two-inch area around the navel), the front of the middle thighs, the upper outer areas of the buttocks, or the upper back portion of the upper arms. The injection site should be varied daily. GRANIX should not be injected into an area that is tender, red, bruised, or hard, or that has scars or stretch marks.

2.3 Important Administration Instructions for Healthcare Professionals

Hold the syringe assembly by the open sides of the device and remove the needle shield.

Expel any extra volume depending on dose needed.

Inject GRANIX subcutaneously as recommended [see Dosage and Administration (2.2)].

Push the plunger as far as it will go to inject all the medication. Injection of the entire prefilled syringe contents is necessary to activate the needle guard.

With the plunger still pressed all the way down, remove the needle from the skin.

Slowly let go of the plunger and allow the empty syringe to move up inside the device until the entire needle is guarded.

Discard the syringe assembly in approved containers.

3 DOSAGE FORMS AND STRENGTHS

GRANIX is a clear, colorless, preservative-free solution available as:

Prefilled Syringe:

Injection: 300 mcg/0.5 mL solution in single-dose prefilled syringe

Injection: 480 mcg/0.8 mL solution in single-dose prefilled syringe

Vial:

Injection: 300 mcg/mL solution in single-dose vial

Injection: 480 mcg/1.6 mL (300 mcg/mL) solution in single-dose vial

4 CONTRAINDICATIONS

GRANIX is contraindicated in patients with a history of serious allergic reactions to filgrastim products or pegfilgrastim products [see Warnings and Precautions (5.3)].

5 WARNINGS AND PRECAUTIONS

5.1 Splenic Rupture

Splenic rupture, including fatal cases, can occur following administration of filgrastim products. Evaluate patients who report upper abdominal or shoulder pain for an enlarged spleen or splenic rupture. Discontinue GRANIX if splenic rupture is suspected or confirmed.

5.2 Acute Respiratory Distress Syndrome

Acute respiratory distress syndrome (ARDS) can occur in patients receiving filgrastim products. Evaluate patients who develop fever and lung infiltrates or respiratory distress after receiving GRANIX, for ARDS. Discontinue GRANIX in patients with ARDS.

5.3 Serious Allergic Reactions

Serious allergic reactions, including anaphylaxis, can occur in patients receiving GRANIX. Reactions can occur on initial exposure. The administration of antihistamines‚ steroids‚ bronchodilators‚ and/or epinephrine may reduce the severity of the reactions. Permanently discontinue GRANIX in patients with serious allergic reactions. Do not administer GRANIX to patients with a history of serious allergic reactions to filgrastim or pegfilgrastim.

5.4 Sickle Cell Disorders

Severe and sometimes fatal sickle cell crises can occur in patients with sickle cell disorders receiving filgrastim products. Discontinue GRANIX if sickle cell crisis occurs.

5.5 Glomerulonephritis

Glomerulonephritis can occur in patients receiving filgrastim products. The diagnoses were based on azotemia, hematuria (microscopic and macroscopic), proteinuria, and renal biopsy. Generally, events of glomerulonephritis resolved after dose reduction or discontinuation of the filgrastim product. If glomerulonephritis is suspected, evaluate for cause. If causality is likely, consider dose reduction or interruption of GRANIX.

5.6 Capillary Leak Syndrome

Capillary leak syndrome (CLS) can occur in patients receiving filgrastim products and is characterized by hypotension, hypoalbuminemia, edema and hemoconcentration. Episodes vary in frequency, severity and may be life-threatening if treatment is delayed. Patients who develop symptoms of capillary leak syndrome should be closely monitored and receive standard symptomatic treatment, which may include a need for intensive care.

5.7 Potential for Tumor Growth Stimulatory Effects on Malignant Cells

The granulocyte colony-stimulating factor (G‑CSF) receptor through which GRANIX acts has been found on tumor cell lines. The possibility that GRANIX acts as a growth factor for any tumor type, including myeloid malignancies and myelodysplasia, diseases for which GRANIX is not approved, cannot be excluded.

5.8 Myelodysplastic Syndrome and Acute Myeloid Leukemia in Patients with Breast and Lung Cancer

Patients with Severe Chronic Neutropenia

Confirm the diagnosis of SCN before initiating GRANIX therapy.

MDS and AML have been reported to occur in the natural history of congenital neutropenia without cytokine therapy. Cytogenetic abnormalities, transformation to MDS, and AML have also been observed in patients treated with GRANIX for SCN. Based on available data including a postmarketing surveillance study, the risk of developing MDS and AML appears to be confined to the subset of patients with congenital neutropenia. Abnormal cytogenetics and MDS have been associated with the eventual development of myeloid leukemia. The effect of GRANIX on the development of abnormal cytogenetics and the effect of continued GRANIX administration in patients with abnormal cytogenetics or MDS are unknown. Monitor patients for signs and symptoms of MDS/AML in these settings. If a patient with SCN develops abnormal cytogenetics or myelodysplasia‚ the risks and benefits of continuing GRANIX should be carefully considered.

Patients with Breast and Lung Cancer

MDS and AML have been associated with the use of GRANIX in conjunction with chemotherapy and/or radiotherapy in patients with breast and lung cancer. Monitor patients for signs and symptoms of MDS/AML in these settings.

5.9 Leukocytosis

White blood cell counts of 100‚000/mm^3 or greater were observed in approximately 2% of patients receiving filgrastim products at dosages above 5 mcg/kg/day. In patients with cancer receiving GRANIX as an adjunct to myelosuppressive chemotherapy‚ to avoid the potential risks of excessive leukocytosis‚ it is recommended that GRANIX therapy be discontinued if the ANC surpasses 10‚000/mm^3 after the chemotherapy-induced ANC nadir has occurred. Monitor CBCs at least twice weekly during therapy. Dosages of GRANIX that increase the ANC beyond 10‚000/mm^3 may not result in any additional clinical benefit. In patients with cancer receiving myelosuppressive chemotherapy‚ discontinuation of filgrastim products therapy usually resulted in a 50% decrease in circulating neutrophils within 1 to 2 days‚ with a return to pretreatment levels in 1 to 7 days.

5.10 Simultaneous Use with Chemotherapy and Radiation Therapy Not Recommended

The safety and efficacy of filgrastim products, including GRANIX, given simultaneously with cytotoxic chemotherapy have not been established. Because of the potential sensitivity of rapidly dividing myeloid cells to cytotoxic chemotherapy‚ do not use GRANIX in the period 24 hours before through 24 hours after the administration of cytotoxic chemotherapy [see Dosage and Administration (2.2)].

The safety and efficacy of GRANIX have not been evaluated in patients receiving concurrent radiation therapy. Avoid the simultaneous use of GRANIX with chemotherapy and radiation therapy.

5.11 Nuclear Imaging

Increased hematopoietic activity of the bone marrow in response to growth factor therapy has been associated with transient positive bone-imaging changes. Consider this when interpreting bone-imaging results.

5.12 Aortitis

Aortitis has been reported in patients receiving another filgrastim product. It may occur as early as the first week after start of therapy. Manifestations may include generalized signs and symptoms such as fever, abdominal pain, malaise, back pain, and increased inflammatory markers (e.g., c‑reactive protein and white blood cell count). Consider aortitis in patients who develop these signs and symptoms without known etiology. Discontinue GRANIX if aortitis is suspected.

5.13 Alveolar Hemorrhage

Alveolar hemorrhage manifesting as pulmonary infiltrates and hemoptysis requiring hospitalization has been reported in healthy donors undergoing peripheral blood progenitor cell (PBPC) collection treated with another filgrastim product. Hemoptysis resolved with discontinuation of filgrastim. The use of GRANIX for PBPC mobilization in healthy donors is not an approved indication.

6 ADVERSE REACTIONS

The following potential serious adverse reactions are discussed in greater detail in other sections of the labeling:

- Splenic Rupture [see Warnings and Precautions (5.1)]
- Acute Respiratory Distress Syndrome [see Warnings and Precautions (5.2)]
- Serious Allergic Reactions [see Warnings and Precautions (5.3)]
- Sickle Cell Disorders [see Warnings and Precautions (5.4)]
- Glomerulonephritis [see Warnings and Precautions (5.5)]
- Capillary Leak Syndrome [see Warnings and Precautions (5.6)]
- Potential for Tumor Growth Stimulatory Effects on Malignant Cells [see Warnings and Precautions (5.7)]
- Myelodysplastic Syndrome and Acute Myeloid Leukemia [see Warnings and Precautions (5.8)]
- Leukocytosis [see Warnings and Precautions (5.9)]
- Simultaneous Use with Chemotherapy and Radiation Therapy Not Recommended [see Warnings and Precautions (5.10)]
- Aortitis [see Warnings and Precautions (5.12)]
- Alveolar Hemorrhage [see Warnings and Precautions (5.13)]

6.1 Clinical Trials Experience

Because clinical trials are conducted under widely varying conditions, adverse reaction rates observed in the clinical trials of a drug cannot be directly compared to rates in the clinical trials of another drug and may not reflect the rates observed in clinical practice.

Adverse Reactions in Adult Patients

GRANIX clinical trials safety data are based upon the results of three randomized clinical trials in patients receiving myeloablative chemotherapy for breast cancer (N=348), lung cancer (N=240) and non-Hodgkin’s lymphoma (N=92). In the breast cancer study, 99% of patients were female, the median age was 50 years, and 86% of patients were Caucasian. In the lung cancer study, 80% of patients were male, the median age was 58 years, and 95% of patients were Caucasian. In the non-Hodgkin’s lymphoma study, 52% of patients were male, the median age was 55 years, and 88% of patients were Caucasian. In all three studies a placebo (Cycle 1 of the breast cancer study only) or a non-U.S.-approved filgrastim product were used as controls. Both GRANIX and the non-U.S.-approved filgrastim product were administered at 5 mcg/kg subcutaneously once daily beginning one day after chemotherapy for at least five days and continued to a maximum of 14 days or until an ANC of ≥10,000 x 10^6/L after nadir was reached.

Bone pain was the most frequent treatment-emergent adverse reaction that occurred in at least 1% or greater in patients treated with GRANIX at the recommended dose and was numerically two times more frequent than in the placebo group. The overall incidence of bone pain in Cycle 1 of treatment was 3.4% (3.4% GRANIX, 1.4% placebo, 7.5% non-U.S.-approved filgrastim product).

Leukocytosis
In clinical studies, leukocytosis (WBC counts > 100,000 x 10^6/L) was observed in less than 1% patients with non-myeloid malignancies receiving GRANIX. No complications attributable to leukocytosis were reported in clinical studies.

Additional Adverse Reactions
Other adverse reactions known to occur following administration of filgrastim products include myalgia, headache, vomiting, cutaneous vasculitis and thrombocytopenia.

Adverse Reactions in Pediatric Patients
GRANIX clinical trials safety data in pediatric patients are based upon the results of one single-arm clinical trial in 50 pediatric patients who received myelosuppressive chemotherapy for treatment of solid tumors without marrow involvement [see Use in Special Populations (8.4)]. In this study, GRANIX was administered at 5 mcg/kg subcutaneously once daily beginning one day after chemotherapy. The most common (>5%) adverse reactions included thrombocytopenia (34%), pyrexia (8%), pain in extremity (6%), headache (6%) and diarrhea (6%).

6.2 Postmarketing Experience

The following adverse reactions have been identified during post-approval use of GRANIX. Because these reactions are reported voluntarily from a population of uncertain size, it is not always possible to reliably estimate their frequency or establish a causal relationship to drug exposure.

- Sweet’s syndrome (acute febrile neutrophilic dermatosis), asthenia, diarrhea, and fatigue

8 USE IN SPECIFIC POPULATIONS

8.1 Pregnancy

Risk Summary

The limited published data on filgrastim product use during pregnancy are insufficient to inform a drug-associated risk. In animal reproduction studies, administration of tbo-filgrastim to pregnant rabbits during organogenesis resulted in increased spontaneous abortion and fetal malformations at systemic exposures 50 to 90 times the human exposure expected at the recommended human dose (see Data). GRANIX should be used during pregnancy only if the potential benefit justifies the potential risk to the fetus.

The estimated background risk of major birth defects and miscarriage for the indicated population(s) are unknown. All pregnancies have a background risk of birth defect, loss, or other adverse outcomes. In the U.S. general population, the estimated background risk of major birth defects and miscarriage in clinically recognized pregnancies is 2% to 4% and 15% to 20%, respectively.

Data

Animal Data

In an embryofetal developmental study, pregnant rabbits were administered subcutaneous doses of tbo-filgrastim during the period of organogenesis at 1, 10 and 100 mcg/kg/day. Increased abortions were evident in rabbits treated with tbo-filgrastim at 100 mcg/kg/day. This dose was maternally toxic as demonstrated by reduced body weight. Other embryofetal findings at this dose level consisted of post-implantation loss‚ decrease in mean live litter size and fetal weight, and fetal malformations such as malformed hind limbs and cleft palate. The dose of 100 mcg/kg/day corresponds to a systemic exposure (AUC) of approximately 50 to 90 times the exposures observed in patients treated with the clinical tbo-filgrastim dose of 5 mcg/kg/day.

8.2 Lactation

No data are available regarding the presence of tbo-filgrastim in human milk, the effects of the drug on the breastfed child, or the effects of the drug on milk production. Another filgrastim product was detected in human milk for up to 3 days after filgrastim administration. Because of the potential for serious adverse reactions in the breastfed child, including splenic rupture, acute respiratory distress syndrome and serious allergic reactions, advise patients not to breastfeed during treatment with GRANIX and for 2 weeks after the last dose.

8.4 Pediatric Use

The safety and effectiveness of GRANIX have been established for pediatric patients 1 month to < 17 years old (no data for the age group < 1 month old). Use of GRANIX in these age groups is supported by evidence from adequate and well-controlled studies of GRANIX in adults [see Clinical Studies (14)] with additional safety and pharmacokinetics data from a single-arm trial of 50 pediatric patients with solid tumors treated with GRANIX for chemotherapy-induced neutropenia. The 50 pediatric patients had a median age of 9.2 years (range, 1.4 to 15.9 years); 2 were infants (1 month to < 2 years old), 30 were children (2 to < 12 years old), and 18 were adolescents (12 to < 17 years old). The pharmacokinetics and safety profile of GRANIX in the pediatric population were similar to those seen in adults [see Adverse Reactions (6.1), Clinical Pharmacology (12.3)].

8.5 Geriatric Use

Among 677 cancer patients enrolled in clinical trials of GRANIX, a total of 111 patients were 65 years of age and older, and 14 patients were 75 years and older. No overall differences in safety or effectiveness were observed between patients age 65 and older and younger patients.

11 DESCRIPTION

GRANIX (tbo-filgrastim) is a non-glycosylated recombinant methionyl human granulocyte colony-stimulating growth factor (r-metHuG-CSF) manufactured by recombinant DNA technology using the bacterium strain E coli K802. It has a molecular weight of approximately 18.8 kDa and is composed of 175 amino acids. The endogenous human G-CSF is glycosylated and does not have the additional methionine amino acid residue in its NH2 terminal end.

The product is a sterile, clear, colorless, preservative-free solution containing tbo-filgrastim, glacial acetic acid, sorbitol, polysorbate 80, sodium hydroxide, and Water for Injection. The product is available in single-dose prefilled syringes that contain either 300 mcg or 480 mcg of tbo-filgrastim at a fill volume of 0.5 mL or 0.8 mL, respectively and single-dose vials that contain either 300 mcg or 480 mcg of tbo-filgrastim at a fill volume of 1 mL or 1.6 mL, respectively. See table below for product composition of each presentation.

Product Composition
 | 300 mcg/0.5 mL Syringe | 480 mcg/0.8 mL Syringe | 300 mcg/1 mL Vial | 480 mcg/1.6 mL Vial
Tbo-filgrastim | 300 mcg | 480 mcg | 300 mcg | 480 mcg
Glacial Acetic Acid | 0.3 mg | 0.48 mg | 0.6 mg | 0.96 mg
Polysorbate 80 | 0.0275 mg | 0.044 mg | 0.055 mg | 0.088 mg
Sorbitol | 25 mg | 40 mg | 50 mg | 80 mg
Sodium Hydroxide | q.s. to pH 4.2 | q.s. to pH 4.2 | q.s. to pH 4.2 | q.s. to pH 4.2
Water for Injection | q.s. to 0.5 mL | q.s. to 0.8 mL | q.s. to 1 mL | q.s. to 1.6 mL
q.s. = quantity sufficient to make

12 CLINICAL PHARMACOLOGY

12.1 Mechanism of Action

Tbo-filgrastim is a human granulocyte colony-stimulating factor (G-CSF) produced by recombinant DNA technology. Tbo-filgrastim binds to G-CSF receptors and stimulates proliferation of neutrophils. G-CSF is known to stimulate differentiation commitment and some end-cell functional activation, which increases neutrophil counts and activity.

12.2 Pharmacodynamics

The time to the maximum ANC level was between 3 to 5 days and returned to baseline by 21 days following completion of chemotherapy. Doubling the tbo-filgrastim subcutaneous dose from 5 mcg/kg to 10 mcg/kg resulted in a 16% to 19% increase in the maximum ANC level and a 33% to 36% increase in the area under the effect curve for ANC.

Cardiac Electrophysiology

At an intravenous dose of 5 mcg/kg, tbo-filgrastim did not prolong the QT interval to any clinically relevant extent.

12.3 Pharmacokinetics

Tbo-filgrastim exhibits nonlinear pharmacokinetics. Increasing the dose of subcutaneous GRANIX from 5 to 10 mcg/kg resulted in an approximate 2.5-fold increase in the maximum serum concentration (Cmax) and 3.0-fold increase in the area under the curve (AUC). In adult patients enrolled across three studies, subcutaneous GRANIX 5 mcg/kg resulted in median time to maximal serum tbo-filgrastim concentrations (Tmax) within 4 to 6 hours. Geometric mean [coefficient of variation (CV%)] serum Cmax was 20 to 31 ng/mL [24% to 65%] within 4 to 6 hours. Geometric mean serum tbo-filgrastim area under the curve (AUC0-12h) ranged from 151 to 227 ng/mL*h [24% to 60%]. No accumulation in serum tbo-filgrastim concentrations was observed after multiple dosing.

Absorption

The absolute bioavailability of 5 mcg/kg subcutaneous tbo-filgrastim was 33%.

Metabolism/Elimination

Tbo-filgrastim clearance is primarily dependent on G-CSF receptor-mediated clearance which can be saturated by high serum concentrations of tbo-filgrastim and diminished in neutropenia. The median serum elimination half-life of tbo-filgrastim (5 mcg/kg sc) was 3.0 to 3.5 hours.

Specific Populations

No sex-related differences were observed.

Pediatric Patients:

The geometric mean [coefficient of variation (CV%)] of Cmax was 18 ng/mL (56%) and AUC0-12h was 130 ng*hr/mL (52%) following subcutaneous administration of GRANIX 5 mcg/kg in 49 pediatric patients (1.4 to 15.9 years) after chemotherapy. No clinically relevant differences in the pharmacokinetics of GRANIX were observed between infants, children and adolescents.

Patients with Renal or Hepatic Impairment:

Mild renal impairment (creatinine clearance 60 to 89 mL/min by Cockcroft-Gault) had no effect on tbo-filgrastim pharmacokinetics. The pharmacokinetics in patients with moderate and severe renal impairment has not been studied. The pharmacokinetics in patients with hepatic impairment has not been studied.

12.6 Immunogenicity

The observed incidence of anti-drug antibodies is highly dependent on the sensitivity and specificity of the assay. Differences in assay methods preclude meaningful comparisons of the incidence of anti-drug antibodies in the studies described below with the incidence of anti-drug antibodies in other studies, including those of GRANIX or of other filgrastim products.

While available data suggest that 1.4% of patients developed binding antibodies to filgrastim, the nature and specificity of these antibodies has not been adequately studied. Because of the low occurrence of anti- drug antibodies, the effect of these antibodies on the pharmacokinetics, pharmacodynamics, safety, and/or effectiveness of GRANIX is unknown.

Cytopenias resulting from an antibody response to exogenous growth factors have been reported on rare occasions in patients treated with other recombinant growth factors.

13 NONCLINICAL TOXICOLOGY

13.1 Carcinogenesis, Mutagenesis, Impairment of Fertility

Carcinogenicity and genetic toxicology studies have not been conducted with tbo-filgrastim.

A fertility study was not conducted with tbo-filgrastim. Toxicology studies of up to 26 weeks in rats or monkeys did not reveal findings in male or female reproductive organs that would suggest impairment of fertility.

14 CLINICAL STUDIES

The efficacy of GRANIX was evaluated in a multinational, multicenter, randomized and controlled Phase 3 study in 348 chemotherapy-naive patients with high-risk stage II, stage III, or stage IV breast cancer receiving doxorubicin (60 mg/m^2) and docetaxel (75 mg/m^2) comparing GRANIX to placebo and a non-U.S.-approved filgrastim product as controls. The median age of the patients was 50 years (range 25 to 75 years) with 99% female and 86% Caucasian.

GRANIX, placebo, and the non-U.S.-approved filgrastim product were administered at 5 mcg/kg subcutaneously once daily beginning one day after chemotherapy for at least five days and continued to a maximum of 14 days or until an ANC of ≥10,000 x 10^6/L after nadir was reached.

GRANIX was superior to placebo in duration of severe neutropenia (DSN) with a statistically significant reduction in DSN (1.1 days vs. 3.8 days, p < 0.0001).

16 HOW SUPPLIED/STORAGE AND HANDLING

GRANIX solution for injection is supplied as a single-dose, preservative-free clear solution, in either a vial or, a prefilled syringe made from Type I glass which has a permanently attached stainless steel needle. The active substance is tbo-filgrastim.

Prefilled Syringes (UltraSafe Passive® Needle Guard)

GRANIX 300 mcg/0.5 mL: Each prefilled syringe contains 300 mcg of tbo-filgrastim in 0.5 mL solution with a blue plunger in:

- Pack of 1 with a safety needle guard in blister: NDC 63459-910-11
- Packs of 10 with a safety needle guard in blisters: NDC 63459-910-15

GRANIX 480 mcg/0.8 mL: Each prefilled syringe contains 480 mcg of tbo-filgrastim in 0.8 mL solution with a clear plunger in:

- Pack of 1 with a safety needle guard in blister: NDC 63459-912-11
- Packs of 10 with a safety needle guard in blisters: NDC 63459-912-15

Prefilled Syringes

GRANIX 300 mcg/0.5 mL: Each prefilled syringe contains 300 mcg of tbo-filgrastim in 0.5 mL solution with a blue plunger in:

- Pack of 1 without a safety needle guard (for patients and caregivers): NDC 63459-910-17
- Packs of 5 without a safety needle guard (for patients and caregivers): NDC 63459-910-36

GRANIX 480 mcg/0.8 mL: Each prefilled syringe contains 480 mcg of tbo-filgrastim in 0.8 mL solution with a clear plunger in:

- Pack of 1 without a safety needle guard (for patients and caregivers): NDC 63459-912-17
- Packs of 5 without a safety needle guard (for patients and caregivers): NDC 63459-912-36

Vials

GRANIX 300 mcg/mL: Each vial contains 300 mcg of tbo-filgrastim in 1 mL solution.

- Packs of 10 single-dose vials: (NDC 63459-918-59)

GRANIX 480 mcg/1.6 mL (300 mcg/mL): Each vial contains 480 mcg of tbo-filgrastim in 1.6 mL solution.

- Packs of 10 single-dose vials: (NDC 63459-920-59)

GRANIX and all its components are not made with natural rubber latex [see Dosage and Administration (2.2)].

Store GRANIX in a refrigerator at 36°F to 46°F (2°C to 8°C). Protect from light. Within its shelf life, the product may be removed from 36°F to 46°F (2°C to 8°C) storage for a single period of up to 5 days between 73°F to 81°F (23°C to 27°C). If not used within 5 days, the product may be returned to 36°F to 46°F (2°C to 8°C) up to the expiration date. Dispose of syringes if stored at room temperature for more than 5 days.

Avoid shaking. The solution should be visually inspected prior to use. Only clear solutions without particles should be used. Exposure to 23°F to 30°F (-1°C to -5°C) for up to 72 hours and temperatures as low as 5°F to -13°F (-15°C to -25°C) for up to 24 hours do not adversely affect the stability of GRANIX.

Single-dose syringe and single-dose vial – discard unused portion. Any unused product or waste material should be disposed of in accordance with local requirements.

If GRANIX gets on the skin, wash the area with soap and water. If GRANIX gets in the eyes, thoroughly flush the exposed eye/eyes with water.

17 PATIENT COUNSELING INFORMATION

Availability of Patient Information and Instructions for Use

Advise all patients and/or caregivers to read the FDA-approved Patient Information. For patients that are candidates for self-administration, assist patients and caregivers in understanding the contents of the Patient Information as well as the GRANIX Instructions for Use that are included with the product, and give them the opportunity to ask questions prior to initiating therapy.

Patient Training

Once it is determined that a patient is an appropriate candidate for self-administration or administration by a caregiver, instruct the patient or caregivers on the proper storage, preparation, and administration technique for GRANIX. Patients should be advised not to skip or change their dose or stop taking GRANIX without talking to their healthcare provider first. Advise the patients to read the FDA-approved Patient Information and Instructions for Use for further information.

Bone Pain

Bone pain is common. Analgesics such as acetaminophen or NSAIDS may be necessary [see Adverse Reactions (6.1)].

Rupture or Enlargement of Spleen

Rupture or enlargement of the spleen may occur, which may be signaled by abdominal pain, left upper quadrant pain, or left shoulder pain. Advise patients to report onset of pain in these areas to their doctor immediately [see Warnings and Precautions (5.1)].

Dyspnea

Dyspnea with or without fever, progressing to Acute Respiratory Distress Syndrome, may occur. Advise patients to report dyspnea immediately to their doctor [see Warnings and Precautions (5.2)].

Allergic Reactions

Serious allergic reactions, including anaphylaxis, rash, and urticaria: Patients should report such reactions immediately to their doctor [see Warnings and Precautions (5.3)].

Sickle Cell Disorders

In patients with sickle cell disorders, sickle cell crisis and death has occurred. Discuss the potential risks and benefits for patients with sickle cell disorders prior to the administration of GRANIX [see Warnings and Precautions (5.4)].

Glomerulonephritis

Symptoms may include swelling of the face or ankles, dark colored urine or blood in the urine, or a decrease in urine production. Advise patients to report signs or symptoms of glomerulonephritis to their physician immediately [see Warnings and Precautions (5.5)].

Myelodysplastic Syndrome and Acute Myeloid Leukemia

There may be an increased risk of Myelodysplastic Syndrome and/or Acute Myeloid Leukemia in patients with congenital neutropenia who receive GRANIX and in patients with breast and lung cancer who receive GRANIX in conjunction with chemotherapy and/or radiation therapy. Symptoms of MDS and AML may include tiredness, fever, and easy bruising or bleeding. Advise patients to report to their physician signs and symptoms of MDS/AML [see Warnings and Precautions (5.8)].

Pregnancy

Inform patients not to become pregnant while receiving GRANIX. If pregnancy occurs, advise patients of the possibility of fetal harm [see Use in Specific Populations (8.1)].

Lactation

Advise women to avoid breastfeeding during treatment with GRANIX and for 2 weeks after the final dose. [see Use in Specific Populations (8.2)].

See FDA-approved Patient Labeling (Patient Information) and Instructions for Use.

TBO-010

©2023 Cephalon, Inc., a wholly owned subsidiary of Teva Pharmaceutical Industries Ltd. All rights reserved.

Manufactured by:
UAB Teva Baltics
Vilnius, Lithuania

U.S. License No. 1803

Distributed by:
Teva Pharmaceuticals USA, Inc.
North Wales, PA 19454

Product of Israel

PATIENT INFORMATION
GRANIX (GRAN-icks)
(tbo-filgrastim)
injection, for subcutaneous use

What is GRANIX?

GRANIX is a prescription medicine:

- used in adults and children 1 month of age and older with certain types of cancer (non-myeloid malignancies), who are receiving chemotherapy that affects the bone marrow
- given to help decrease the length of time that the number of certain white blood cells (neutrophils) are very low (severe neutropenia). Neutrophils are white blood cells that are important in fighting bacterial infections.

It is not known if GRANIX is safe and effective in children younger than 1 month of age.

Do not take GRANIX if you have had a serious allergic reaction to filgrastim products or pegfilgrastim products.

Before you receive GRANIX, tell your healthcare provider about all of your medical conditions, including if you:

- have a sickle cell disorder
- have kidney problems
- plan to have bone scans or tests
- are pregnant or plan to become pregnant. It is not known if GRANIX will harm your unborn baby. You should not become pregnant during treatment with GRANIX.
- are breastfeeding or plan to breastfeed. It is not known if GRANIX passes into your breast milk. Do not breastfeed during treatment with GRANIX and for 2 weeks after the final dose.

Tell your healthcare provider about all the medicines you take, including prescription and over-the-counter medicines, vitamins, and herbal supplements.

How will I receive GRANIX?

- GRANIX is given by an injection under your skin (subcutaneous) by a healthcare provider. Your healthcare provider may decide injections can be given at home by you or your caregiver. If GRANIX is given at home, see the detailed “Instructions for Use” that comes with your GRANIX for information on how to prepare and inject a dose of GRANIX.
- Your healthcare provider will show you and your caregiver how to prepare and inject GRANIX before you use it.
- Your healthcare provider will tell you how much GRANIX to inject and when to inject it. Do not stop using GRANIX or change your dose unless your healthcare provider tells you to.
- GRANIX injections are usually given 1 time each day until your white blood cell count returns to normal.
- Your first dose of GRANIX is given at least 24 hours after you receive your chemotherapy.
- Do not inject GRANIX within 24 hours before your next dose of chemotherapy.
- Your healthcare provider will test your blood before your chemotherapy and during treatment with GRANIX.
- If GRANIX gets on your skin or your caregiver’s skin, wash the area with soap and water.
- If GRANIX gets in your eyes or your caregiver’s eyes, flush the eyes well with water.

What are the possible side effects of GRANIX?

GRANIX can cause serious side effects, including:

- Spleen rupture. Your spleen may become enlarged and can rupture. A ruptured spleen can cause death. Call your healthcare provider right away if you have pain in your left upper stomach (abdomen)-area or your left shoulder during treatment with GRANIX.
- A serious lung problem called acute respiratory distress syndrome (ARDS). Call your healthcare provider or get emergency medical help right away if you have shortness of breath with or without fever, trouble breathing, or a fast rate of breathing.
- Serious allergic reactions. GRANIX can cause serious allergic reactions. These reactions can cause a rash over your whole body, shortness of breath, wheezing, dizziness, swelling around your mouth or eyes, fast heart rate, and sweating. If you have any of these symptoms, stop using GRANIX and call your healthcare provider or get emergency help right away.
- Sickle cell crisis. You may have a serious sickle cell crisis, which could lead to death, if you have a sickle cell disorder and use GRANIX. Call your healthcare provider right away if you have symptoms of sickle cell crisis such as pain or difficulty breathing.
- Kidney injury (glomerulonephritis). GRANIX can cause kidney injury. Call your healthcare provider right away if you develop any of the following symptoms:
  - swelling of your face or ankles
  - blood in your urine or dark colored urine
  - you urinate less than usual
- Increased white blood cell count (leukocytosis). Your healthcare provider will check your blood during treatment with GRANIX.
- Capillary Leak Syndrome. GRANIX can cause fluid to leak from blood vessels into your body’s tissues. This condition is called “Capillary Leak Syndrome” (CLS). CLS can quickly cause you to have symptoms that may become life-threatening. Get emergency medical help right away if you develop any of the following symptoms:
  - swelling or puffiness and are urinating less than usual
  - trouble breathing
  - swelling of your stomach-area (abdomen) and feeling of fullness
  - dizziness or feeling faint
  - a general feeling of tiredness
- Myelodysplastic syndrome (MDS) and acute myeloid leukemia (AML).
  - GRANIX may increase the risk of developing a precancerous condition called MDS or a type of blood cancer called AML in people who were born with low white blood cell counts (congenital neutropenia).
  - If you have breast cancer or lung cancer, when GRANIX is used with chemotherapy and radiation therapy, or with radiation therapy only, you may have an increased risk of developing MDS or AML.
  - Symptoms of MDS and AML may include tiredness, fever, and easy bruising or bleeding.
  - Call your healthcare provider if you develop any of these symptoms during treatment with GRANIX.
- Inflammation of the aorta (aortitis). Inflammation of the aorta (the large blood vessel which transports blood from the heart to the body) has been reported in patients who received another filgrastim product. Symptoms may include fever, abdominal pain, feeling tired, and back pain. Call your healthcare provider if you experience these symptoms.

Your healthcare provider may decrease your dose, temporarily stop, or permanently stop treatment with GRANIX if you have certain side effects.

The most common side effect of GRANIX is bone pain.

The most common side effects of GRANIX in children include:

- decreased platelet count
- fever
- pain in the arms and legs

- headache
- diarrhea

These are not all of the possible side effects of GRANIX.

Call your doctor for medical advice about side effects. You may report side effects to FDA at 1-800-FDA-1088.

How should I store GRANIX?

- Store GRANIX in the refrigerator between 36˚F to 46˚F (2˚C to 8˚C).
- Keep GRANIX away from light to protect it. If your GRANIX prefilled syringe or vial comes in a carton, keep it in the carton until you are ready to use it, to protect from light.
- Do not shake.
- Take GRANIX out of the refrigerator 30 minutes before use and allow it to reach room temperature before preparing an injection.
- GRANIX can be left at room temperature for up to 5 days. If not used within 5 days, return GRANIX back to the refrigerator. Throw away (dispose of) GRANIX that has been left at room temperature for more than 5 days.
- After you inject your dose, throw away (dispose of) any unused GRANIX left in the syringe or vial. Do not save unused GRANIX in the syringe or the vial for later use.

Keep GRANIX and all medicines out of the reach of children.

General information about the safe and effective use of GRANIX

Medicines are sometimes prescribed for purposes other than those listed in Patient Information leaflets. Do not use GRANIX for a condition for which it was not prescribed. Do not give GRANIX to other people, even if they have the same symptoms you have. It may harm them. You can ask your healthcare provider or pharmacist for information about GRANIX that is written for health professionals.

What are the ingredients in GRANIX?

Active ingredient: tbo-filgrastim

Inactive ingredients: glacial acetic acid, sorbitol, polysorbate 80, sodium hydroxide, and Water for Injection

Manufactured by:
UAB Teva Baltics
Vilnius, Lithuania

U.S. License No. 1803

Distributed by:
Teva Pharmaceuticals USA, Inc.
North Wales, PA 19454

Product of Israel

TBOPL-008

©2023 Cephalon, Inc., a wholly owned subsidiary of Teva Pharmaceutical Industries Ltd. All rights reserved.

For more information, call 1-800-896-5855.

This Patient Information has been approved by the U.S. Food and Drug Administration Revised: 11/2023

INSTRUCTIONS FOR USE - Prefilled Syringe

GRANIX (GRAN-icks)
(tbo-filgrastim)
for subcutaneous injection
Single-Dose Prefilled Syringe

Important:

Read the Prescribing information and Patient Package insert for important information about GRANIX.

About the GRANIX syringe

Depending on the prescription that your healthcare provider gave you, you will receive a syringe that provides a dose of either 0.1 mL to 0.5 mL or 0.1 mL to 0.8 mL. If you are prescribed a dose over 0.8 mL, two syringes will be required to reach your prescribed dose. Your healthcare provider will determine how many syringes and the correct dose in milliliters (mL) you will need to give based on your body weight. You should continue to give GRANIX daily until your healthcare provider informs you that your white blood cell count has returned to normal.

Make sure you understand the following:

- How to store your syringes.
- How to read the syringe markings.
- How to adjust the amount of GRANIX in the syringe for your prescribed dose.
- How to prepare and give the injection.

Do not shake syringes.

Do not remove the needle cap until you are ready to inject.

Do not re-use a syringe. The syringe is for single-use only.

Your first dose of GRANIX is given at least 24 hours after you receive your chemotherapy.

Do not inject GRANIX within 24 hours before your next dose of chemotherapy.

Dosing schedule

Inject your total daily dose 1 time each day as prescribed by your healthcare provider, starting at least 24 hours (1 day) after the end of your chemotherapy cycle.

You should continue to give GRANIX daily until your white blood cell count returns to normal.

How to store your GRANIX syringes

- Store GRANIX in the refrigerator between 36°F to 46°F (2°C to 8°C).
- Store GRANIX in the original carton to protect it from light.
- Do not shake.
- Take GRANIX out of the refrigerator 30 minutes before use and allow it to reach room temperature before preparing an injection.
- GRANIX syringes can be left at room temperature for a single period of up to 5 days, and if not used can be returned to the refrigerator. Throw away (dispose of) any GRANIX syringes that have been left at room temperature for more than 5 days.
- After you inject your dose, throw away (dispose of) any unused GRANIX left in the syringe. Do not save unused GRANIX in the syringe for later use.

Keep GRANIX and all medicines out of the reach of children.

Determining how many syringes you need for your daily dose

- If your prescribed daily dose is 0.5 mL or less, use 1 syringe.
- If your prescribed daily dose is 0.8 mL or less, use 1 syringe.
- If your prescribed daily dose is more than 0.8 mL you will need to prepare 2 syringes in order to match your prescribed dose:
  - Adjust your first syringe to 0.8 mL.
  - Adjust your second syringe to the additional amount required to make up your total prescribed dose.
  - Make sure the amounts in both syringes add up to your prescribed dose (See the table to the right to determine how much medicine should be in each syringe).

For example: If your prescribed dose is 1 mL you would prepare 1 syringe with 0.8 mL and a second syringe with 0.2 mL.

Important: When using 2 syringes always adjust the first syringe to 0.8 mL.

How to read the syringe markings

What the markings on the syringe mean:

The syringe is labeled in 0.1 mL unit increments from 0.1 mL to 0.8 mL. There is a line next to each 0.1 mL unit increment.

To read the dose scale always hold the syringe with the needle-end facing up so that 0.1 mL is at the top and 0.8 mL is at the bottom.

How to adjust the medicine level for your prescribed dose

- When setting your dose, (See 2C) you will line up the top edge of the grey rubber stopper with the line on the syringe scale that matches your prescribed dose.
- Note: The top edge of the grey rubber stopper is the edge directly below the dome at the top of the stopper.

Do not use the top of the cone or the middle or lower edges of the grey stopper to measure your dose.

Injection steps (follow the steps below for each day of dosing)

1. Prepare for injection

1A Each time you inject a dose gather the following supplies:

- GRANIX syringe(s)
- Alcohol swabs
- Paper towel
- Cotton ball or gauze pad
- Adhesive Bandage, if needed
- Sharps disposal container (hard-walled container for discarding syringes)

Note: GRANIX and all of the parts of the prefilled syringe do not contain natural rubber latex.

1B Take the carton with the syringe(s) out of the refrigerator

1C Check the label and the expiration date on the side of the carton

Important: Do not inject if:

- “GRANIX® (tbo-filgrastim)” is not listed on the carton.
- The expiration date on the syringe label has passed.

1D Remove the syringe(s) from the carton

Open the carton by breaking the tamper proof seal and lifting the lid. Remove the number of syringes required for your daily dose by grasping each at the middle of the syringe body.

After removing your required number of syringes, place the carton back in the refrigerator.

1E Look carefully at the syringe(s) and the medicine

Hold the syringe body and check to make sure it is not damaged.

Inspect the medicine in the syringe. GRANIX should be a clear liquid.

Important: Do not inject if:

- GRANIX® (tbo-filgrastim) is not listed on the syringe label.
- The medicine is cloudy, discolored, or foamy.
- The medicine contains lumps, flakes, or particles.

1F Wait 30 minutes for the syringe(s) to warm to room temperature

Wait 30 minutes for GRANIX to naturally warm to room temperature. This will provide a more comfortable injection.

1G Wash your hands

When ready to inject, wash your hands with soap and warm water and dry thoroughly with a clean towel.

1H Choose an injection site

The recommended injection sites are:

If you are self-injecting:

Stomach-area (abdomen): Except for a 2-inch area around the navel (belly button).

Thighs: Top or middle area of thighs.

If a caregiver is injecting GRANIX for you:

Arms: Fleshy areas on upper, back part of the arm.

Upper hip or buttock: Fleshy areas around the back of the upper hips and upper sides of the buttocks.

If 2 injections will be performed, then the second injection should be at least 1 inch away from the first injection.

Choose Injection Site

Do not inject into areas that are tender, red, bruised, hard, or have scars or stretch marks.

Important:

- You should select a different injection site each time you give yourself an injection.
- If you want to use the same injection site for a dose requiring 2 injections, make sure the second injection site is at least 1 inch away from the first injection site.

1I Clean the injection site using an alcohol swab

Allow site to dry for 5-10 seconds to avoid stinging.

If giving 2 injections, then the distance between the 2 injection sites should be at least 1 inch apart.

Do not touch or blow on site after cleaning.

2. Adjust medicine level for your prescribed dose

2A Remove the needle cap from the syringe

Place a paper towel on the table.

To remove the needle cap, hold the body of the syringe firmly with 1 hand (with the needle facing away from you).

Pull the needle cap straight off, extending your hand away from the needle.

Note: Throw away the needle cap in a sharps disposal container.

Do not recap the needle now or after the injection.

2B Hold the syringe upright and tap

Hold the syringe upright (needle pointing up), as shown.

Gently tap the barrel with your fingers to make sure any air bubbles rise to the top.

2C Slowly and carefully adjust the medicine level

Hold the syringe with the needle pointing up and slightly away from you, as shown. Make sure you can easily see the syringe markings and numbers.

Holding the plunger as shown, very slowly and carefully push the plunger up until the top edge of the grey rubber stopper is even with the line that corresponds to your prescribed dose.

Note:

- If GRANIX gets on your skin, wash your skin with soap and water.
- If GRANIX get in your eyes, flush well with water.

Note: If you accidentally removed too much GRANIX, contact your healthcare provider before giving your injection.

3. INJECT MEDICATION

3A Pinch skin

The illustration below is an example only

Use your free hand to firmly pinch the skin you previously cleaned.

3B Insert the needle at a 45 to 90 degree angle

Hold the body of the syringe between your thumb and index finger.

Use a quick motion to fully insert the needle straight into the pinched skin at a 45 to 90 degree angle.

When the needle is inserted, you can release the pinched skin.

Do not hold or push on the plunger while inserting the needle into the skin.

3C Push the plunger down to inject all of the GRANIX

Use your finger to gently push down on the plunger.

When the plunger head is as far down as it will go, all of the GRANIX has been injected. When done, gently remove the needle from the skin.

3D Throw away (dispose of) used syringe

Put your used needles and syringes in a FDA-cleared sharps disposal container right away after use. Do not throw away (dispose of) loose needles and syringes in your household trash.

If you do not have a FDA-cleared sharps disposal container, you may use a household container that is:

- made of a heavy-duty plastic,
- can be closed with a tight-fitting, puncture-resistant lid, without sharps being able to come out,
- upright and stable during use,
- leak-resistant, and
- properly labeled to warn of hazardous waste inside the container.

When your sharps disposal container is almost full, you will need to follow your community guidelines for the right way to dispose of your sharps disposal container. There may be state or local laws about how you should throw away used needles and syringes. For more information about safe sharps disposal, and for specific information about sharps disposal in the state that you live in, go to the FDA’s website at: http://www.fda.gov/safesharpsdisposal.

Do not dispose of your used sharps disposal container in your household trash unless your community guidelines permit this. Do not recycle your used sharps disposal container.

3E Treat the injection site if needed and wash your hands

If you see drops of blood at the injection site, you can press a cotton ball or gauze over the injection site for several seconds to stop the bleeding.

Apply bandage, if needed.

When you are finished, wash your hands with soap and warm water and dry thoroughly with a clean towel.

4. Repeat the injection steps with the second syringe (If dose is more than 0.8 mL)

If your dose is more than 0.8 mL:

- Follow instructions 3A through 3E for injecting.
- Choose a different site for your second injection. If you want to use the same part of your body, make sure the second injection site is at least 1 inch away from the first injection site.

If you have any questions or concerns about your dose of GRANIX or how to prepare and give your injections, call your healthcare provider.

This Instructions for Use has been approved by the U.S. Food and Drug Administration.

Manufactured by:
UAB Teva Baltics
Vilnius, Lithuania

U.S. License No. 1803

Distributed by:
Teva Pharmaceuticals USA, Inc.
North Wales, PA 19454

Product of Israel

Revised: 11/2023

TBOIFU-004

©2023 Cephalon, Inc., a wholly owned subsidiary of Teva Pharmaceutical Industries Ltd. All rights reserved.

GRANIX is a trademark of Teva Pharmaceutical Industries Ltd.

INSTRUCTIONS FOR USE - VIAL

INSTRUCTIONS FOR USE
GRANIX (GRAN-icks)
(tbo-filgrastim)
for subcutaneous injection
Single-Dose Vial

Important:

Read the Prescribing information and Patient Package insert for important information about GRANIX.

Before you use a GRANIX vial, read this important information:

- GRANIX vial is supplied as either 300 mcg in 1 mL solution, or 480 mcg of tbo-filgrastim in 1.6 mL solution. Your healthcare provider will determine which strength of GRANIX to prescribe for you. Your healthcare provider will prescribe the correct number of vials, and the dose in milliliters (mL) that you will need to inject based on your body weight.
- When you receive your vials of GRANIX at the pharmacy, check the label to be sure that the dose strength on the vial matches the dose strength that your healthcare provider prescribed for you. If you are not sure, ask your pharmacist.
- If you are told that more than 1 injection is needed for each dose of GRANIX, the total dose should be divided into two equal parts. Each of the two parts of your dose should be drawn from a separate vial.
- Your healthcare provider will show you how to measure the correct dose of GRANIX before you try to inject it for the first time. This dose will be measured in milliliters (mL).

How to store your GRANIX vial

- Store GRANIX in the refrigerator between 36°F to 46°F (2°C to 8°C).
- Keep GRANIX vials away from light to protect it. If your GRANIX vial comes in a carton, keep it in the carton until you are ready to use it to protect from light.
- Do not freeze.
- Take GRANIX out of the refrigerator 30 minutes before use and allow it to reach room temperature before preparing an injection.
- GRANIX vials can be left at room temperature for a single period of up to 5 days, and if not used can be returned to the refrigerator to use later. Throw away (dispose of) any GRANIX vials that have been left at room temperature for more than 5 days.
- After you inject your dose, properly dispose of any unused GRANIX left in the vial. Do not save unused GRANIX for later use.

Keep GRANIX and all medicines out of the reach of children.

Using your vial

- It is important that you do not try to give the injection unless you or your caregiver has received training from your healthcare provider.
- Make sure that the name GRANIX appears on the carton and vial label.
- Check the label and the expiration date on the side of the carton. Do not use a vial after the expiration date on the label.
- Do not shake the vial.
- Do not use the vial if the medicine is cloudy or discolored, or contains flakes or particles.

Do not inject your first dose of GRANIX until at least 24 hours after you receive your chemotherapy. You should continue to receive GRANIX daily until your healthcare provider tells you that your white blood cell count has returned to normal. Do not inject GRANIX less than 24 hours before your next dose of chemotherapy.

Call your healthcare provider if you have any questions.

Follow the steps below for each day of dosing

STEP 1: Prepare

Step 1A: Remove GRANIX from the refrigerator

Take the GRANIX® (tbo-filgrastim) carton out of the refrigerator. Open the carton by lifting the lid and breaking the seal.

Step 1B: Check the label and the expiration date on the carton

- Check to make sure "GRANIX® (tbo-filgrastim)” is listed on the carton

- Do not use if the expiration date on the carton has passed

Remove the number of vials needed for the daily dose.

Return the carton containing any unused vials to the refrigerator.

Step 1C: Wait 30 minutes for the vials to reach room temperature.

Place the vials of GRANIX on a clean, well-lit flat work surface for about 30 minutes to warm to room temperature. This will help to provide a more comfortable injection.

- Do not try to warm the vial by using a heat source such as hot water or microwave
- Protect the vial from light
- Do not shake the vial
- Use a vial only 1 time.

Step 1D: Inspect the vial

Hold each vial and check to make sure it is not damaged.

Inspect the medicine in the vial. Make sure the medicine in the vial is clear and colorless.

- Check to make sure GRANIX is listed on the vial label.
- Do not use the vial if:

- The medicine is cloudy or discolored, or contains flakes or particles.
- The expiration date on the vial label has passed

- In these cases, use a new vial and call your healthcare provider.

Step 1E: Gather the following supplies needed for each injection and place them on your clean work surface (Figure A):

- 1 GRANIX vial
- 1 disposable syringe and needles
- 2 alcohol swabs
- 1 cotton balls or gauze pad(s)
- 1 adhesive bandage(s), if needed
- 1 sharps disposal container

- Only use disposable syringes and needles that your healthcare provider prescribes.
- Only use the syringes and needles 1 time. Throw away (dispose of) any used syringes and needles in a sharps disposal container.
- You should only use syringes that are marked in tenths of milliliters (mL).
- Your healthcare provider will show you how to measure the correct dose of GRANIX. This dose will be measured in milliliters (mL).

Step 1F: Wash your hands.

When ready to inject, wash your hands well with soap and water, and dry with a clean towel.

Step 2: Get ready

Step 2A: Take the cap off the vial (Figure B). Clean the rubber stopper with 1 alcohol swab.

Step 2B: Check the packaging for the syringe and needle. If the packaging has been open or damaged, do not use that syringe and needle. Throw away (dispose of) that syringe and needle in your sharps disposal container.

Step 2C: Hold the syringe by the barrel with the needle cap pointing up. Carefully pull the needle cap straight off and away from your body (Figure C).

Important: Throw away (Dispose of) the needle cap.

Step 2D: Keep the vial on the flat work surface and insert the needle straight down through the rubber stopper on top of the vial. Do not insert the needle through the rubber stopper more than 1 time (Figure D).

Step 2E: Push the plunger down and inject all the air from the syringe into the vial of GRANIX (Figure D)

Step 2F: Keep the needle in the vial and turn the vial upside down. Make sure that the GRANIX liquid is covering the tip of the needle (Figure E).

Step 2G: Keep the vial upside down and slowly pull back on the plunger to fill the syringe barrel with GRANIX to the correct marking amount (mL) of medicine that matches the dose your healthcare provider prescribed.

Step 2H: Keep the needle in the vial and check for air bubbles in the syringe. If there are air bubbles, gently tap the syringe barrel with your finger until the air bubbles rise to the top. Slowly push the plunger up to push the air bubbles out of the syringe (Figure F).

Step 2I: Keep the tip of the needle in the liquid and pull the plunger back to the number on the syringe barrel that matches your dose. Check again for air bubbles. The air in the syringe will not hurt you, but too large an air bubble can reduce your dose of GRANIX. If there are still air bubbles, repeat the steps above to remove them.

Step 2J: Check again to make sure that you have the correct dose in the syringe. It is important that you use the exact dose prescribed by your healthcare provider. Do not remove the needle from the vial. Lay the vial down on its side with the needle still in the vial while you prepare the injection site (Figure G).

Step 3 – Select and prepare the injection site

Step 3A: Choose an injection site (Figure H)

You can use:

- Stomach-area (abdomen): Except for a 2-inch area around the navel (belly button)

- Thighs: Top or middle area of thighs

- Arms: Fleshy areas on upper, back part of the arm (only if someone else is giving you the injection)
- Upper outer area of your buttocks: Fleshy areas around the back of the upper hips and upper sides of the buttocks (only if someone else if giving you the injection).

- If 2 injections will be performed, then the second injection should be at least 1 inch away from the first injection.

Choose Injection Site

Figure H

Do not inject into areas that are tender, red, bruised, hard, or have scars or stretch marks.

Important:

You should select a different injection site each time you give yourself an injection.

If you want to use the same injection site for a dose requiring 2 injections, make sure the second injection site is at least 1 inch away from the first injection site.

Step 3B: Clean the injection site using a new alcohol swab (Figure I).

Allow site to dry for 5-10 seconds to avoid stinging.

If giving 2 injections, then the distance between the 2 injection sites should be at least 1 inch apart.

- Do not touch this area again before injecting.

Step 4 –Inject medication

Step 4A: Remove the prepared syringe and needle from the vial.

Step 4B: With your other hand, pinch the skin around the injection site to create a firm surface (Figure J).

Important: Keep skin pinched while inserting the needle.

Step 4C: Insert the needle at a 45 to 90 degree angle (Figure K)

- Hold the body of the syringe between your thumb and index finger.
- Use a quick motion to fully insert the needle straight into the pinched skin at a 45 to 90 degree angle.

- When the needle is inserted, you can release the pinched skin.

- Do not hold or push on the plunger while inserting the needle into the skin.

Step 4D Push the plunger down to inject all of the GRANIX (Figure L)

- Use your finger to gently push down on the plunger.
- When the plunger head is as far down as it will go, all of the GRANIX has been injected. When done, gently remove the needle from the skin.

Step 4E: Throw away (dispose of) used needle and syringe

- Put your used needles and syringes in a FDA-cleared sharps disposal container right away after use. Do not throw away (dispose of) loose needles and syringes in your household trash.
- If you do not have a FDA-cleared sharps disposal container, you may use a household container that is:
  - made of a heavy-duty plastic,
  - can be closed with a tight-fitting, puncture-resistant lid, without sharps being able to come out,
  - upright and stable during use,
  - leak-resistant, and
  - properly labeled to warn of hazardous waste inside the container.
- When your sharps disposal container is almost full, you will need to follow your community guidelines for the right way to dispose of your sharps disposal container. There may be state or local laws about how you should throw away used needles and syringes. For more information about safe sharps disposal, and for specific information about sharps disposal in the state that you live in, go to the FDA’s website at: http://www.fda.gov/safesharpsdisposal.
- Do not dispose of your used sharps disposal container in your household trash unless your community guidelines permit this. Do not recycle your used sharps disposal container.

Step 4F: Treat the injection site if needed and wash your hands.

If you see drops of blood at the injection site, you can press a cotton ball or gauze over the injection site for several seconds to stop the bleeding.

Apply bandage, if needed.

When you are finished, wash your hands with soap and water (Figure M).

Step 4G: Repeat steps 1E through 4F with a new vial of GRANIX if your healthcare provider instructs you that your dose is more than 1 vial.

If you have any questions or concerns about your dose of GRANIX or how to prepare and give your injections, call your healthcare provider.

This Instructions for Use has been approved by the U.S. Food and Drug Administration.

Manufactured by:
UAB Teva Baltics
Vilnius, Lithuania

U.S. License No. 1803

Distributed by:
Teva Pharmaceuticals USA, Inc.
North Wales, PA 19454

Product of Israel

Revised: 11/2023

TBOIFUV-003

©2023 Cephalon, Inc., a wholly owned subsidiary of Teva Pharmaceutical Industries Ltd. All rights reserved.

GRANIX is a trademark of Teva Pharmaceutical Industries Ltd.

Package/Label Display Panel 63459-910-11

NDC 63459-910-11

Rx only

Granix® (tbo-filgrastim) Injection

300 mcg/0.5 mL

For Subcutaneous Use Only

A recombinant Granulocyte Colony-Stimulating Factor (rG-CSF) derived from E Coli

300 mcg/0.5 mL

For Healthcare Professional Use Only

1 Single-dose prefilled syringe with a safety needle guard

Discard unused portion

Package/Label Display Panel, 63459-910-17

NDC 63459-910-17

Granix® (tbo-filgrastim) Injection

300 mcg/0.5 mL

For Subcutaneous Use Only

A recombinant Granulocyte Colony-Stimulating Factor (rG-CSF) derived from E Coli

1 Single-dose prefilled syringe WITHOUT a safety needle guard

Rx only

Discard unused portion

300 mcg/0.5 mL

Package/Label Display Panel 63459-912-11

NDC 63459-912-11

Rx only

Granix® (tbo-filgrastim) Injection

480 mcg/0.8 mL

For Subcutaneous Use Only

A recombinant Granulocyte Colony-Stimulating Factor (rG-CSF) derived from E Coli

480 mcg/0.8 mL

For Healthcare Professional Use Only

1 Single-dose prefilled syringe with a safety needle guard

Discard unused portion

Package/Label Display Panel, 63459-912-17

NDC 63459-912-17

Rx only

Granix® (tbo-filgrastim) Injection

480 mcg/0.8 mL

For Subcutaneous Use Only

A recombinant Granulocyte Colony-Stimulating Factor (rG-CSF) derived from E Coli

480 mcg/0.8 mL

For Healthcare Professional Use Only

1 Single-dose prefilled syringe WITHOUT a safety needle guard

Discard unused portion

Package/Label Display Panel, 63459-918-59

NDC 63459-918-59

10 x 300 mcg/mL Single-Dose Vials (containing 1 mL)

Granix (tbo-filgrastim) Injection

300 mcg/mL

For Subcutaneous Use Only.

A recombinant Granulocyte Colony-Stimulating Factor (rG-CSF) derived from E. coli. Discard unused portion.

Rx Only

Package/Label Display Panel, 63459-920-59

NDC 63459-920-59

10 x 480 mcg/1.6 mL Single-Dose Vials

Granix (tbo-filgrastim) Injection

480 mcg/1.6 mL

(300 mg/mL)

For Subcutaneous Use Only. A recombinant Granulocyte Colony-Stimulating Factor (rG-CSF) derived from E. coli. Discard unused portion.

Rx Only